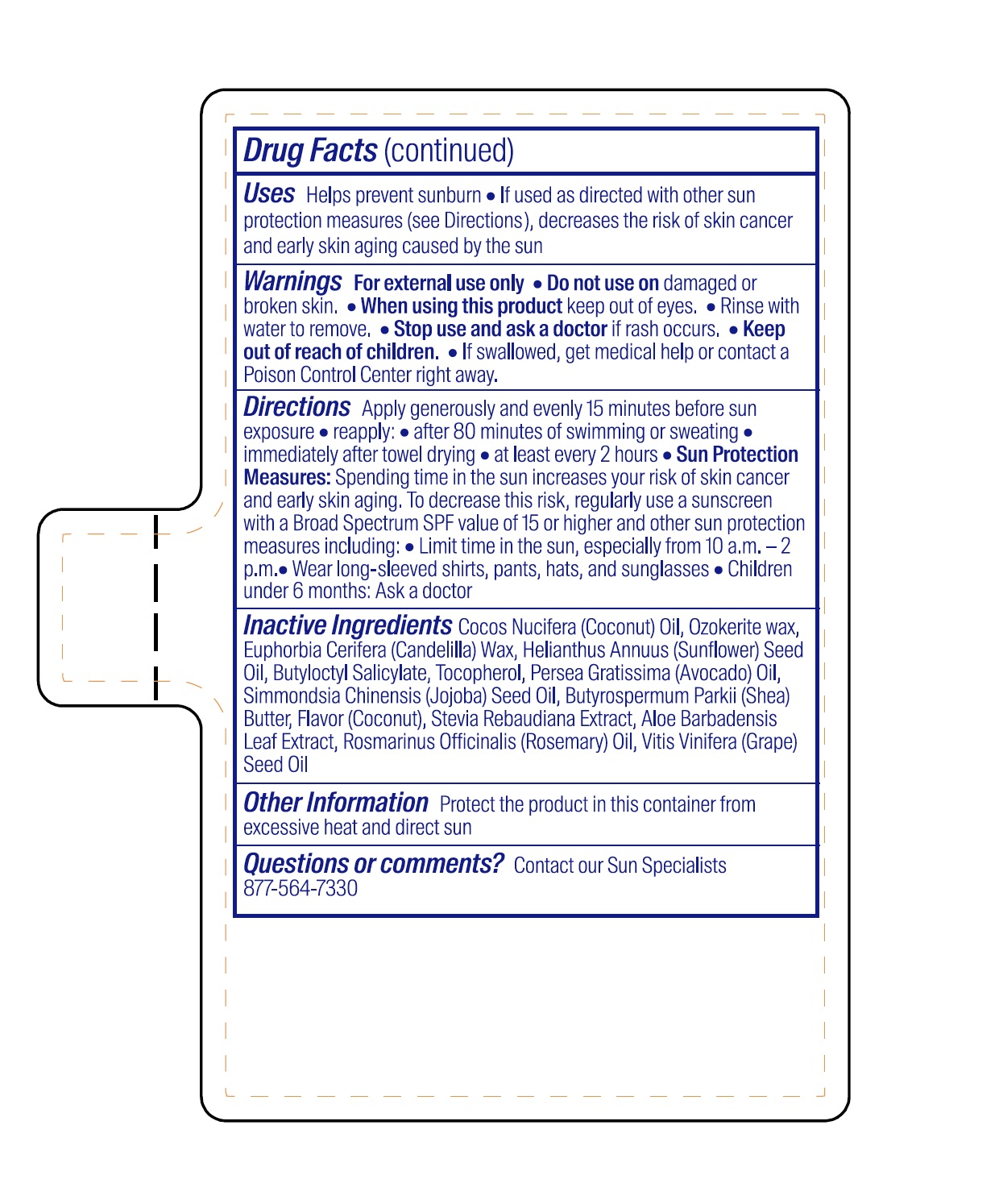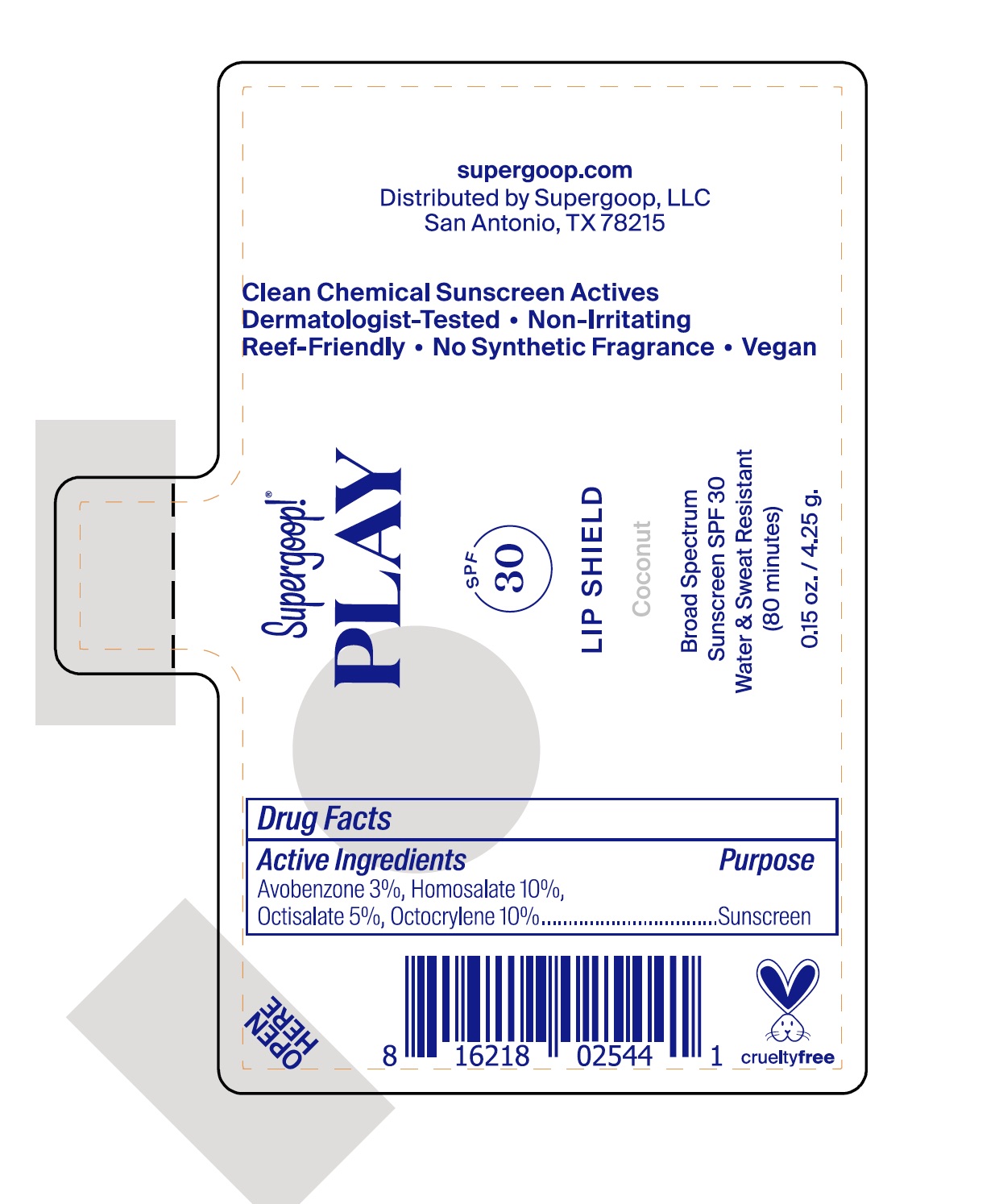 DRUG LABEL: PLAY SPF 30 Lip Shield Coconut
NDC: 75936-156 | Form: GEL
Manufacturer: Supergoop, LLC
Category: otc | Type: HUMAN OTC DRUG LABEL
Date: 20241216

ACTIVE INGREDIENTS: OCTISALATE 5 g/100 g; OCTOCRYLENE 10 g/100 g; AVOBENZONE 3 g/100 g; HOMOSALATE 10 g/100 g
INACTIVE INGREDIENTS: BUTYLOCTYL SALICYLATE; SHEA BUTTER; COCONUT OIL; CANDELILLA WAX; ALOE VERA LEAF; CERESIN; SUNFLOWER OIL; AVOCADO OIL; JOJOBA OIL; TOCOPHEROL; GRAPE SEED OIL; ROSEMARY

PLAY SPF 30 Lip Shield Coconut

ACTIVE INGREDIENT

Avobenzone 3%, Homosalate 10%, Octisalate 5%, Octocrylene 10% .... Purpose Sunscreen

PURPOSE

Uses Helps prevent sunburn

- If used as directed with other sun protection measures (see Directions), decreases the risk of skin cancer acn early skin aging caused by the sun.

Keep out of reach of children. If swallowed, get medical help or contact a Poison Control Center right away.

Stop use and ask a doctor if rash occurs.

WARNINGS

For external use only.

Do not use on damaged or broken skin.

When using this product keep out of eyes. Rinse with water to remove.

DOSAGE AND ADMINISTRATION

Apply generously and evenly 15 minutes before sun exposure.

- reapply: after 80 minutes of swimming or sweating.
- immediately after towel drying
- at least every 2 hours
- Sun Protection Measures: Spending time in the sun increases your skin of skin cancer and early skin aging. To decrease this risk, regularly use a sunscreen with a Broad Spectrum SPF value of 15 or higher and other sun protection measures including:
- Limit time in the sun, especially from 10 a.m. - 2 p.m.
- Wear long-sleeved shirts, pants, hats, and sunglasses
- Children under 6 months: Ask a doctor

INACTIVE INGREDIENT

Butyloctyl Salicylate, Butyrospermum Parkii (Shea) Butter, Cocos Nucifera (Coconut) Oil, Euphorbia Cerifera (Candelila) Wax, Flavor (Coconut), Aloe Barbadensis Leaf Extract, Helianthus Annuus (Sunflower) Seed Oil, Ozokeite Wax, Persea Gratissima (Avocado) Oil, Rosmarinus Officinalis (Rosemary) Leaf Extract, Simmondsia Chinensis (Jojoba) Seed Oil, Stevia Rebaudiana Extract, Tocopherol, Vitis Vinifera (Grape) Seed Oil

STORAGE AND HANDLING

Protect the product in this container from excessive heat and direct sun

PACKAGE LABEL

Supergoop!

PLAY

SPF 30

Lip Shield

Coconut

Broad Spectrum Sunscreen SPF 30

Water & Sweat Resistant

(80 minutes)

0.15 oz. / 4.25 g.